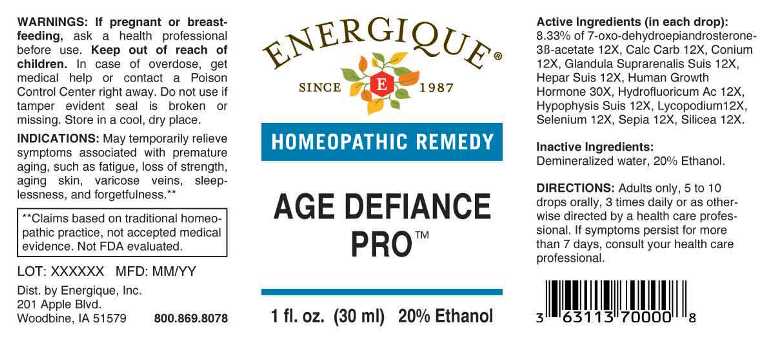 DRUG LABEL: Age Defiance Pro
NDC: 44911-0474 | Form: LIQUID
Manufacturer: Energique, Inc.
Category: homeopathic | Type: HUMAN OTC DRUG LABEL
Date: 20240703

ACTIVE INGREDIENTS: 7-OXODEHYDROEPIANDROSTERONE 3-ACETATE 12 [hp_X]/1 mL; OYSTER SHELL CALCIUM CARBONATE, CRUDE 12 [hp_X]/1 mL; CONIUM MACULATUM FLOWERING TOP 12 [hp_X]/1 mL; SUS SCROFA ADRENAL GLAND 12 [hp_X]/1 mL; PORK LIVER 12 [hp_X]/1 mL; HYDROFLUORIC ACID 12 [hp_X]/1 mL; SUS SCROFA PITUITARY GLAND 12 [hp_X]/1 mL; LYCOPODIUM CLAVATUM SPORE 12 [hp_X]/1 mL; SELENIUM 12 [hp_X]/1 mL; SEPIA OFFICINALIS JUICE 12 [hp_X]/1 mL; SILICON DIOXIDE 12 [hp_X]/1 mL; SOMATROPIN 30 [hp_X]/1 mL
INACTIVE INGREDIENTS: WATER; ALCOHOL

DRUG FACTS:

ACTIVE INGREDIENTS:

(in each drop): 8.33% of 7-Oxo-Dehydroepiandrosterone-3B-Acetate 12X, Calcarea Carbonica 12X, Conium Maculatum 12X, Glandula Suprarenalis Suis 12X, Hepar Suis 12X, Human Growth Hormone 30X, Hydrofluoricum Acidum 12X, Hypophysis Suis 12X, Lycopodium Clavatum 12X, Selenium Metallicum 12X, Sepia 12X, Silicea 12X.

INDICATIONS:

May temporarily relieve symptoms associated with premature aging, such as fatigue, loss of strength, aging skin, varicose veins, sleeplessness and, forgetfulness.**
**Claims based on traditional homeopathic practice, not accepted medical evidence. Not FDA evaluated.

WARNINGS:

If pregnant or breast-feeding, ask a health professional before use.

Keep out of reach of children. In case of overdose, get medical help or contact a Poison Control Center right away.

Do not use if tamper evident seal is broken or missing. Store in a cool, dry place.

Keep out of reach of children. In case of overdose, get medical help or contact a Poison Control Center right away.

DIRECTIONS:

Adults only, 5 to 10 drops orally, 3 times daily or as otherwise directed by a health professional. If symptoms persist for more than 7 days, consult your health care professional.

INDICATIONS:

May temporarily relieve symptoms associated with premature aging, such as fatigue, loss of strength, aging skin, varicose veins, sleeplessness and, forgetfulness.**
**Claims based on traditional homeopathic practice, not accepted medical evidence. Not FDA evaluated.

INACTIVE INGREDIENTS:

Demineralized water, 20% Ethanol.

QUESTIONS:

Dist. by Energique, Inc.

201 Apple Blvd

Woodbine, IA 51579 800.869.8078

PACKAGE LABEL DISPLAY:

ENERGIQUE

SINCE 1987

HOMEOPATHIC REMEDY

AGE DEFIANCE

PRO

1 fl. oz. (30 ml)